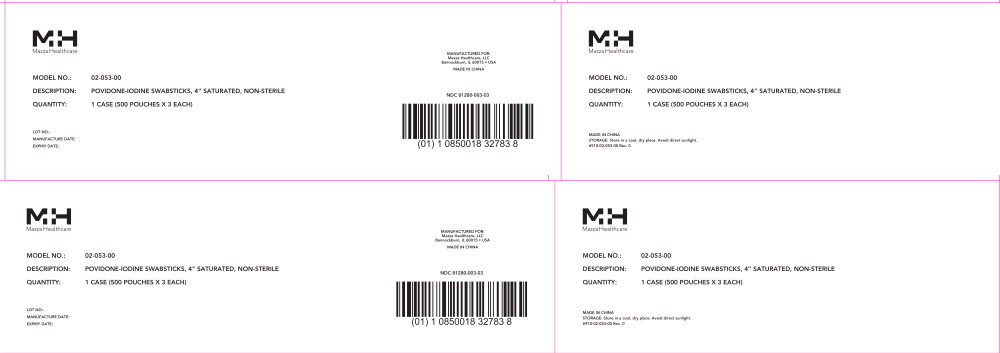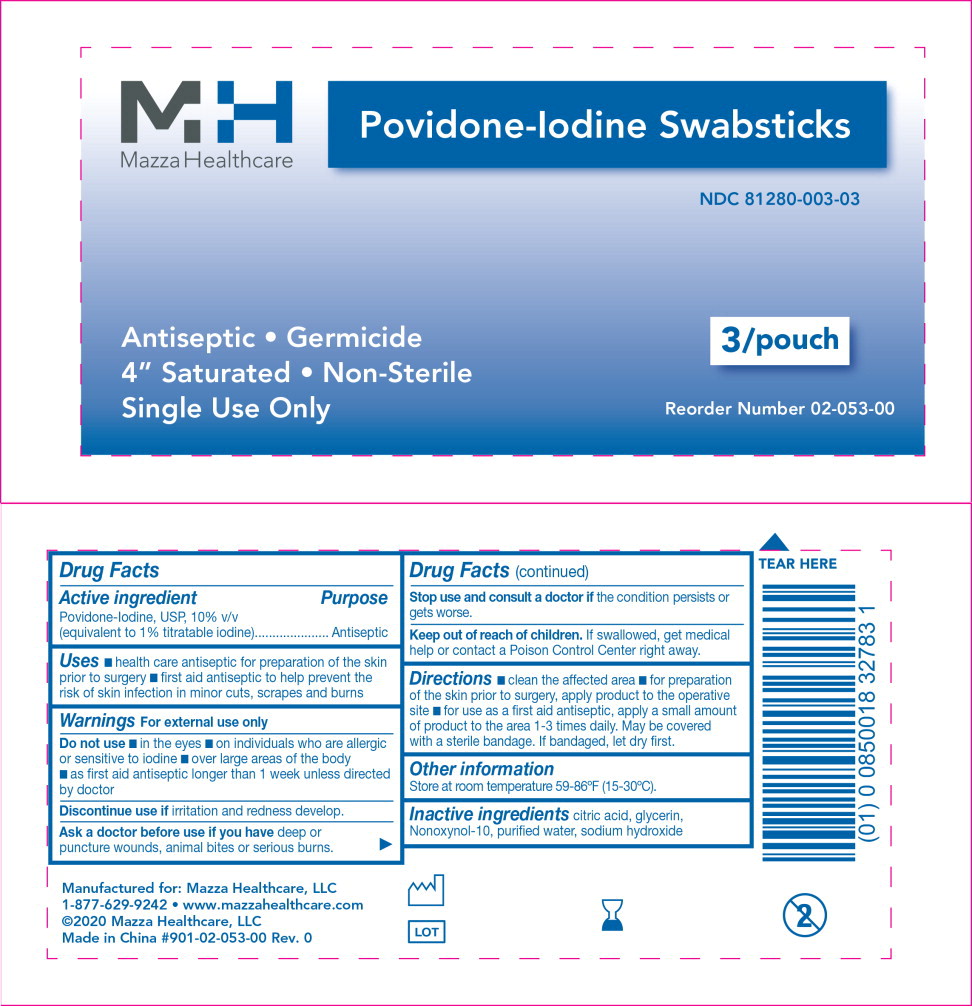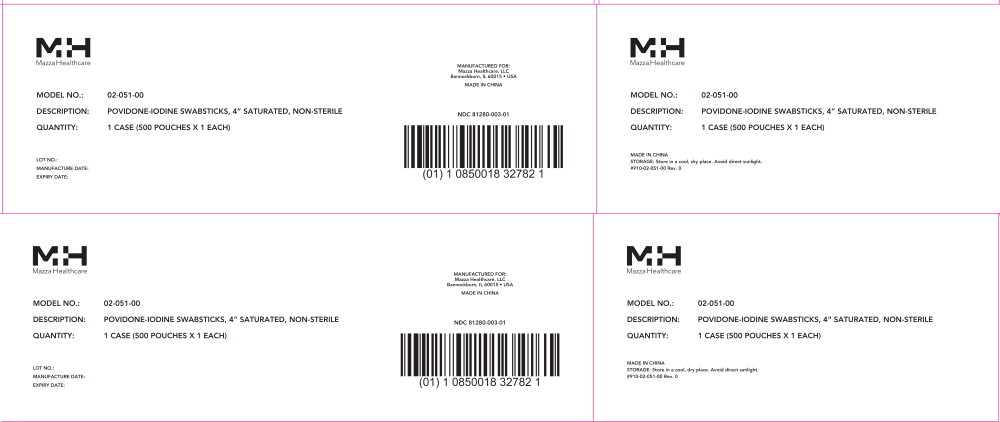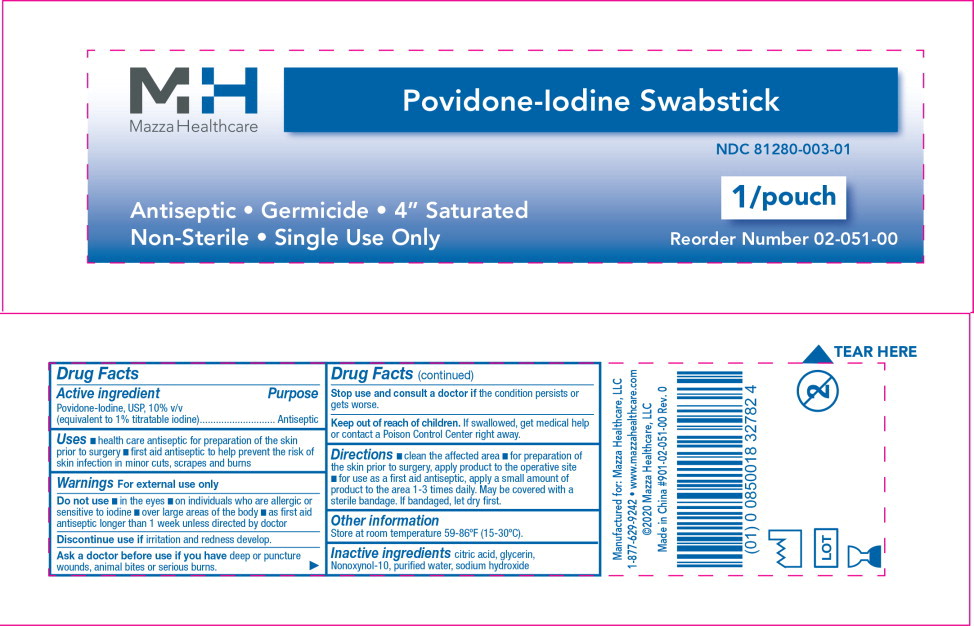 DRUG LABEL: Povidone-Iodine
NDC: 81280-003 | Form: SWAB
Manufacturer: Mazza Healthcare, LLC
Category: otc | Type: HUMAN OTC DRUG LABEL
Date: 20241121

ACTIVE INGREDIENTS: Povidone-Iodine 0.1 mg/1 mL
INACTIVE INGREDIENTS: Citric Acid Monohydrate; Glycerin; Nonoxynol-10; Water; Sodium Hydroxide

Drug Facts

Active ingredient

Povidone-Iodine, USP, 10% v/v
(equivalent to 1% titratable iodine)

Purpose

Antiseptic

Uses

- health care antiseptic for preparation of the skin prior to surgery
- first aid antiseptic to help prevent the risk of skin infection in minor cuts, scrapes and burns

Warnings

For external use only

Do not use

- in the eyes
- on individuals who are allergic or sensitive to iodine
- over large areas of the body
- as first aid antiseptic longer than 1 week unless directed by doctor

Discontinue use if irritation and redness develop.

Ask a doctor before use if you have deep or puncture wounds, animal bites or serious burns.

Stop use and consult a doctor if the condition persists or gets worse.

Keep out of reach of children. If swallowed, get medical help or contact a Poison Control Center right away.

Directions

- clean the affected area
- for preparation of the skin prior to surgery, apply product to the operative site
- for use as a first aid antiseptic, apply a small amount of product to the area 1-3 times daily. May be covered with a sterile bandage. If bandaged, let dry first.

Other information

Store at room temperature 59-86ºF (15-30ºC).

Inactive ingredients

citric acid, glycerin, Nonoxynol-10, purified water, sodium hydroxide

Mazza Healthcare, LLC
1-877-629-9242

Principal Display Panel - 500 Pouch Carton Label

MH

Mazza Healthcare

MODEL NO.: 02-053-00

DESCRIPTION: POVIDONE-IODINE SWABSTICKS, 4” SATURATED, NON-STERILE

QUANTITY: 1 CASE (500 POUCHES X 3 EACH)

LOT NO.:

MANUFACTURE DATE:

EXPIRY DATE:

MANUFACTURED FOR:

Mazza Healthcare, LLC

Bannockburn, IL 60015 • USA

MADE IN CHINA

NDC 81280-003-03

Principal Display Panel - 3 Applicators Pouch Label

MH

Mazza Healthcare

Povidone-Iodine Swabsticks

NDC 81280-003-03

Antiseptic • Germicide • 4” Saturated

Non-Sterile • Single Use Only

3/pouch

Reorder Number 02-053-00

Principal Display Panel - 500 Pouch Carton Label

MH

Mazza Healthcare

MODEL NO.: 02-051-00

DESCRIPTION: POVIDONE-IODINE SWABSTICKS, 4” SATURATED, NON-STERILE

QUANTITY: 1 CASE (500 POUCHES X 1 EACH)

LOT NO.:

MANUFACTURE DATE:

EXPIRY DATE:

MANUFACTURED FOR:

Mazza Healthcare, LLC

Bannockburn, IL 60015 • USA

MADE IN CHINA

NDC 81280-003-01

Principal Display Panel - 1 Applicator Pouch Label

MH

Mazza Healthcare

Povidone-Iodine Swabstick

NDC 81280-003-01

Antiseptic • Germicide • 4” Saturated

Non-Sterile • Single Use Only

1/pouch

Reorder Number 02-051-00